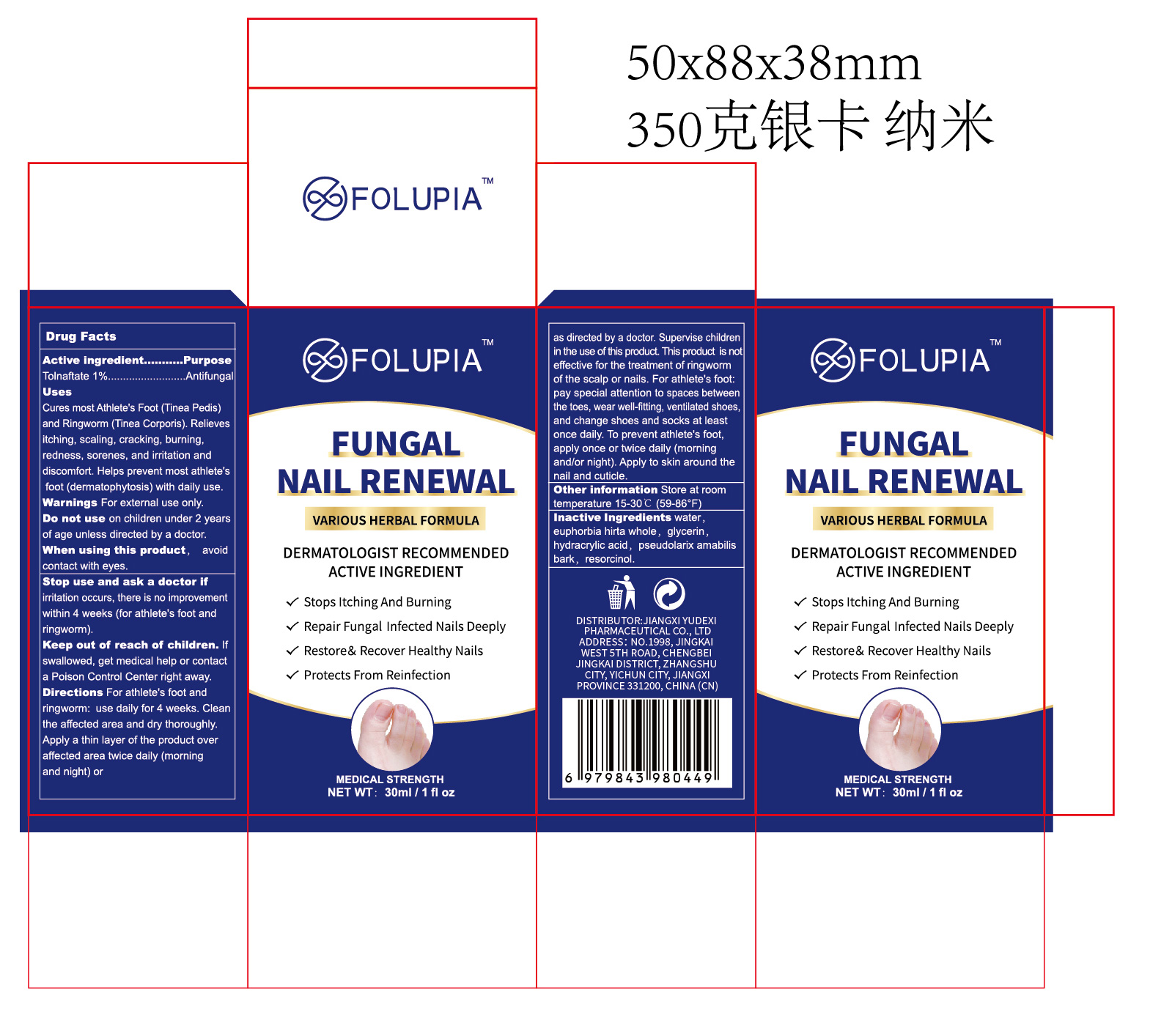 DRUG LABEL: FOLUPIA  FUNGAL NAIL RENEWAL
NDC: 85248-148 | Form: LIQUID
Manufacturer: Jiangxi Yudexi Pharmaceutical Co., LTD
Category: otc | Type: HUMAN OTC DRUG LABEL
Date: 20260227

ACTIVE INGREDIENTS: TOLNAFTATE 1 g/100 mL
INACTIVE INGREDIENTS: EUPHORBIA HIRTA WHOLE; RESORCINOL; HYDRACRYLIC ACID; PSEUDOLARIX AMABILIS BARK; GLYCERIN; WATER

85248-148

Active Ingredient

Tolnaftate 1%

Purpose

Antifungal

Use

Cures most Athlete's Foot (Tinea Pedis) and Ringworm (Tinea Corporis). Relieves itching, scaling, cracking, burning,redness, sorenes, and irritation and discomfort. Helps prevent most athlete's foot (dermatophytosis) with daily use.

Warnings

For external use only.

Do not use

on children under 2 years of age unless directed by a doctor.

When Using

avoid contact with eyes.

Stop Use

irritation occurs, there is no improvement within 4 weeks (for athlete's foot and ringworm).

Ask Doctor

irritation occurs, there is no improvement within 4 weeks (for athlete's foot and ringworm).

Keep Oot Of Reach Of Children

If swallowed, get medical help or contact a Poison Control Center right away.

Directions

For athlete's foot and ringworm: use daily for 4 weeks. Clean the affected area and dry thoroughly. Apply a thin layer of the product over affected area twice daily (morning and night) or as directed by a doctor. Supervise child ren in the use of this product. This product is not effective for the treatment of ringworm of the scalp or nails. For athlete's foot: pay special attention to spaces between the toes, wear well-fitting, ventil ated shoes, and change shoes and socks at least once daily. To prevent athlete's foot, apply once or twice daily (morning and/or night). Apply to skin around the nail and cuticle.

Other information

Store at room temperature 15-30℃ (59-86℉)

Inactive ingredients

water, euphorbia hirta whole, glycerin, hydracrylic acid, pseudolarix amabilis bark, resorcinol.